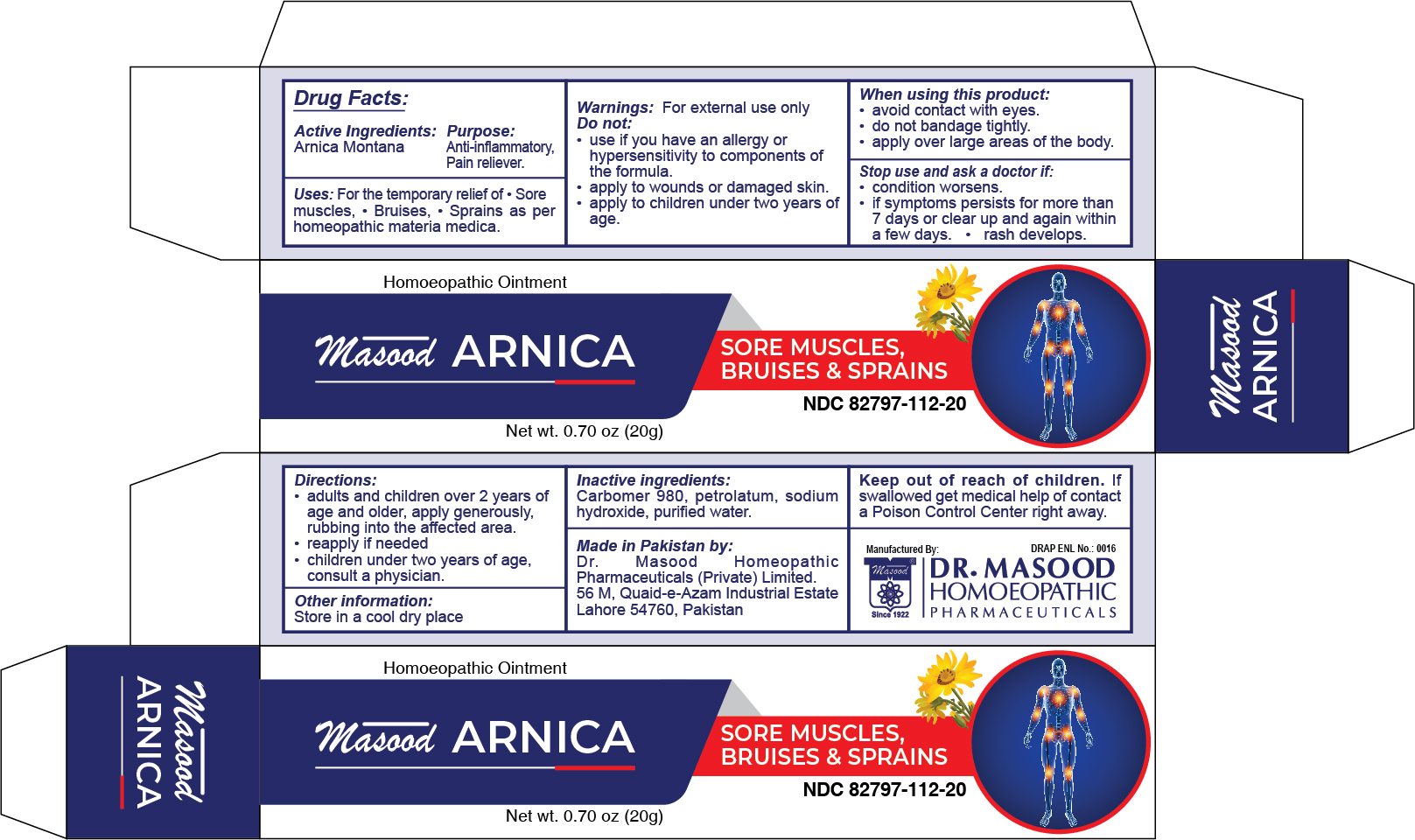 DRUG LABEL: Masood Arnica
NDC: 82797-112 | Form: OINTMENT
Manufacturer: Dr. Masood Homeopathic Pharmaceuticals Private Limited
Category: homeopathic | Type: HUMAN OTC DRUG LABEL
Date: 20240109

ACTIVE INGREDIENTS: ARNICA MONTANA FLOWER 2 g/20 g
INACTIVE INGREDIENTS: SODIUM HYDROXIDE 0.03 g/20 g; PETROLATUM 1 g/20 g; WATER 20 mL/20 g; CARBOMER 980 0.2 g/20 g

Masood Arnica Ointment

Directions:

- adults and children over 2 years of age and older, apply generously, rubbing into the affected area
- reapply if needed
- children under two years of age, consult a physician

Warnings:

For external use only

Do not:

- use if you have an allergy or hypersensitivity to components of the formula
- apply to wounds or damaged skin
- apply to children under two years of age

When using this product:

- avoid contact with eyes
- do not bandage tightly
- apply over large areas of the body

Stop use and ask a doctor if:

- condition worsens
- If symptoms persists for more than 7 days or clear up and again within a few days
- rash develops

If swallowed get medical help of contact a Poison Control Center right away.

Uses:

- For the temporary relief of
- Sores muscles, bruises, sprains as per homeopathic materia medica

Keep out of reach of children.

Active Ingredients

Arnica Montana

Purpose

Anti-inflammatory, Pain reliever

Inactive ingredients:

Carbomer 980, petrolatum, sodium hydroxide, purified water